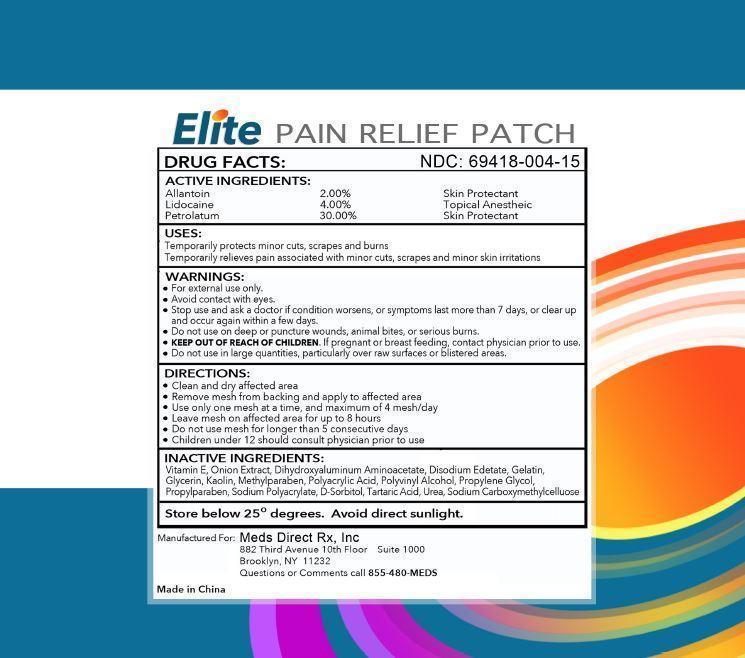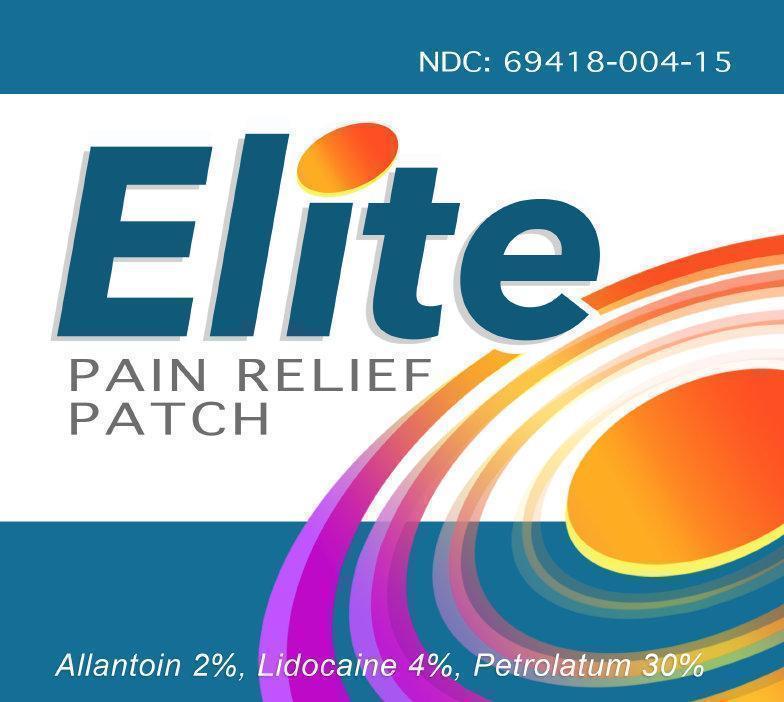 DRUG LABEL: Elite PAIN RELIEF
NDC: 69418-004 | Form: PATCH
Manufacturer: Meds Direct Rx, Inc.
Category: otc | Type: HUMAN OTC DRUG LABEL
Date: 20151118

ACTIVE INGREDIENTS: ALLANTOIN 2 g/100 g; LIDOCAINE 4 g/100 g; PETROLATUM 30 g/100 g
INACTIVE INGREDIENTS: ONION; .ALPHA.-TOCOPHEROL

Elite Pain Relief Patch

ACTIVE INGREDIENTS:

Allantoin 2.00%

Lidocaine 4.00%

Petrolatum 30.00%

PURPOSE

Skin Protectant

Topical Anesthetic

SkinProtectant

USES:

Temporarily protects minor cuts, scrapes and burns

Temporary relief of pain associated with minor cuts, scrapes and minor skin irritations

WARNINGS:

•For external use only.

•Avoid contact with eyes.

•Stop use and ask a doctor if condition worsens, or symptoms last more than 7 days, or clear up and occur again within a few days.

•Do not use on deep or puncture wounds, animal bites, or serious burns.

•If pregnant or breast feeding, contact physician prior to use.

• Do not use in large quantities, particularly over raw surfaces or blistered areas.

KEEP OUT OF REACH OF CHILDREN

DIRECTIONS:

•Clean and dry affected area

•Remove mesh from backing and apply to affected area

•Use only one mesh at a time, and maximum of 4 mesh/day

• Leave mesh on affected area for up to 8 hours

•Do not use mesh for longer than 5 consecutive days

•Children under 12 should consult physician prior to use

INACTIVE INGREDIENTS:

Vitamin E, Onion Extract, Dihydroxyaluminum Aminoacetate, Disodium Edetate, Gelatin, Glycerin, Kaolin, Methylparaben, Polyacrylic Acid, Polyvinyl Alcohol, Propylene Glycol, Propylparaben, Sodium Polyacrylate, D-Sorbitol, Tartaric Acid, Urea, Sodium Carboxymethylcellulose

Store below 25° degrees. Avoid direct sunlight.

Manufactured For:

Meds Direct Rx, Inc

882 Third Avenue 1Oth Floor Suite 1000

Brooklyn, NY 11232

Questions or Comments call 855-480-MEDS

Made in China